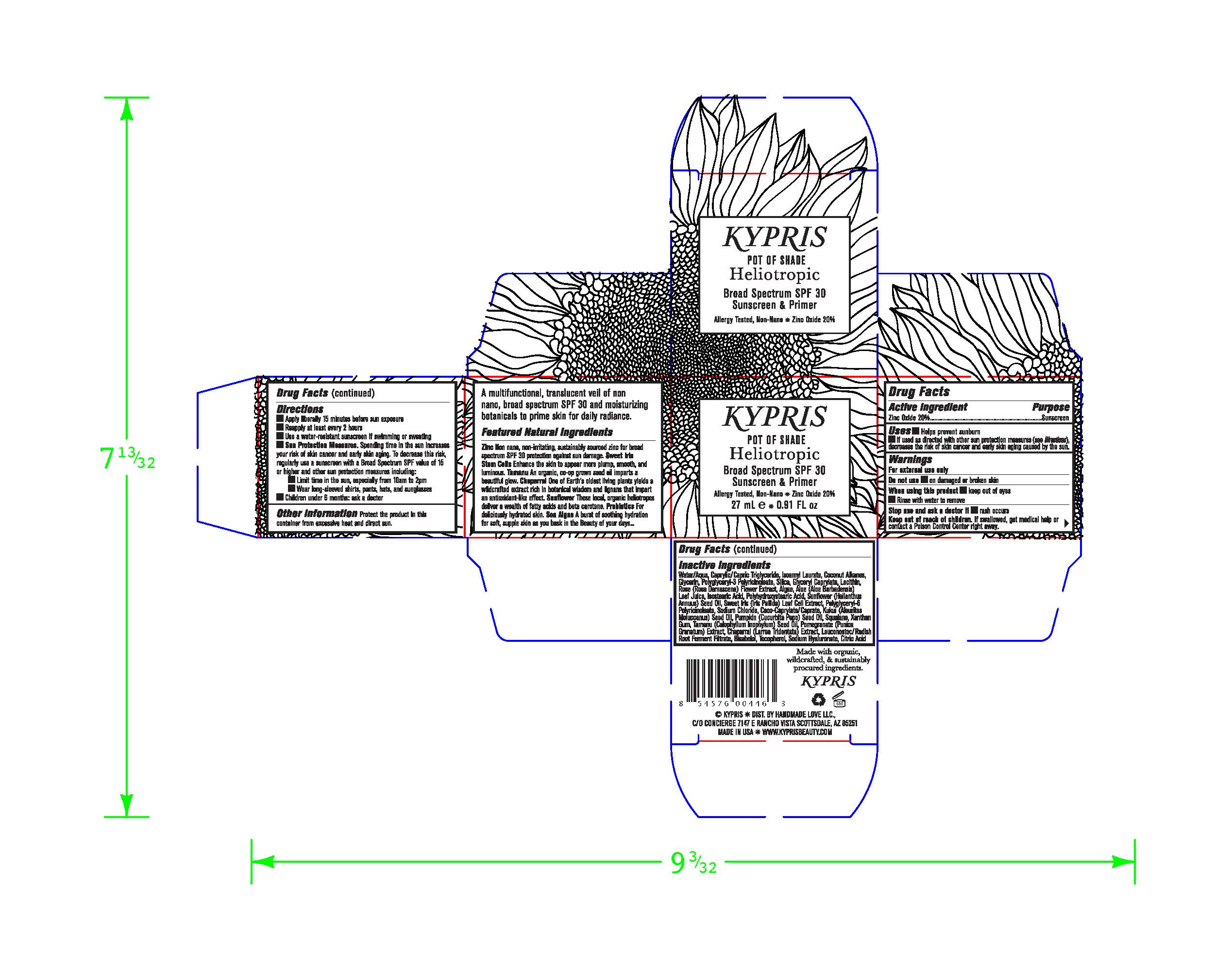 DRUG LABEL: Cream
NDC: 61354-033 | Form: CREAM
Manufacturer: Oxygen Development LLC
Category: otc | Type: HUMAN OTC DRUG LABEL
Date: 20230210

ACTIVE INGREDIENTS: ZINC OXIDE 19.72 mg/100 mg
INACTIVE INGREDIENTS: COCONUT ALKANES; WATER; MEDIUM-CHAIN TRIGLYCERIDES; ISOAMYL LAURATE; POLYHYDROXYSTEARIC ACID (2300 MW); SODIUM CHLORIDE; SILICON DIOXIDE; GLYCERYL CAPRYLATE; ISOSTEARIC ACID; ROSA X DAMASCENA FLOWER; SUNFLOWER OIL; POLYGLYCERYL-6 POLYRICINOLEATE; LECITHIN, SOYBEAN; POLYGLYCERYL-3 PENTARICINOLEATE; GLYCERIN

KYPRIS POT OF SHADE HELIOTROPIC BROAD SPECTRUM SPF30 SUNSCREEN & PRIMER

Active Ingredients

Zinc Oxide 20%

Purpose

Sunscreen

uses

Help prevent sunburns

if used as directed with other sun protection mesures (see Directions), decreases the risk of skin cancer and early aging caused by the sun.

Warnings

For external use only.

Do not use on damaged on broken skin.

When using this product, keep out of eyes. Rinse with water to remove.

Stop use

stop use and ask a doctor if rash occurs

Keep out of reach of children. If swallowed, get medical help or contact Poison Control Center right away.

Directions

Apply liberally 15 minutes before sun exposure.
Reapply at least every two hours
Use a water resistant sunscreen if swimming or sweating.

Sun Protection Measures. Spending time in the sun increases you risk of skin cancer and early skin aging. To decrease this risk, regularly use a sunscreen with a Board Spectrum SPF value 15 or higher and other sun protection measure including:

Limit time in the sun, especially from 10am to 2 pm

Wear long-sleeved shirt, pants, hats, and sunglasses

Children under 6 months: ask a doctor

Other information

Protect the product in this container from excessive heat and direct sun.

INACTIVE INGREDIENT

Water/Aqua, Caprylic/Capric Triglyceride, Isoamyl Laurate, Coconut Alkanes, Glycerin, Polyglyceryl-3 Polyricinoleate, Silica, Glyceryl Caprylate, Lecithin, Rose (Rosa Damascena) Flower Extract, Algae, Aloe (Aloe Barbadensis) Leaf Juice, Isostearic Acid, Polyhydroxystearic Acid, Sunflower (Helianthus Annuus) Seed Oil, Sweet Iris (Iris Pallida) Leaf Cell Extract, Polyglyceryl-6 Polyricinoleate, Sodium Chloride, Coco-Caprylate/Caprate, Kukui (Aleurites Moluccanus) Seed Oil, Pumpkin (Cucurbita Pepo) Seed Oil, Squalane, Xanthan Gum, Tamanu (Calophyllum Inophylum) Seed Oil, Pomegranate (Punica Granatum) Extract, Chaparral (Larrea Tridentata) Extract, Leuconostoc/Radish Root Ferment Filtrate, Bisabolol, Tocopherol, Sodium Hyaluronate, Citric Acid

Secondary package

27 ml 61354-033-01